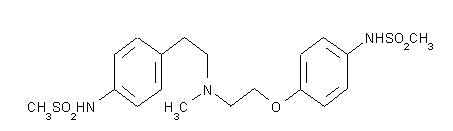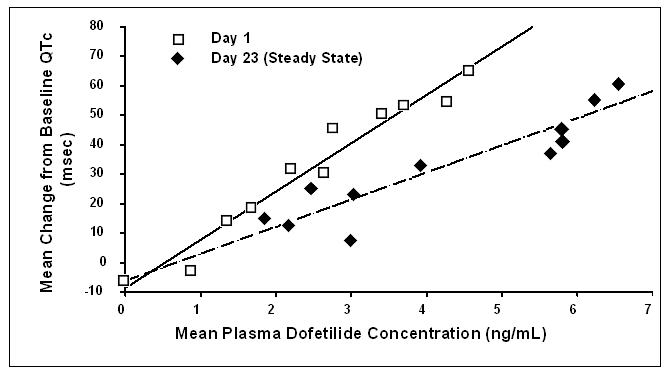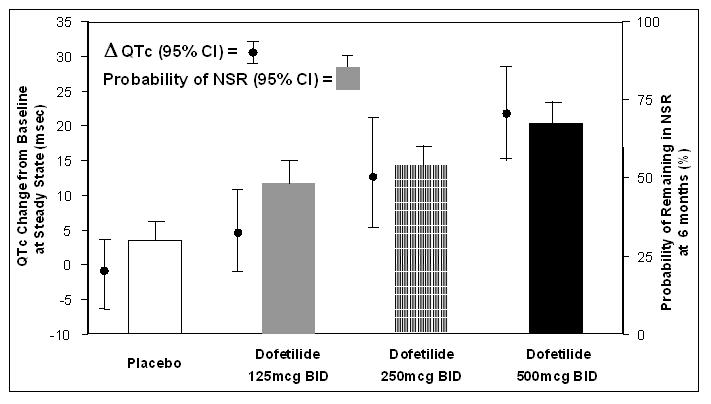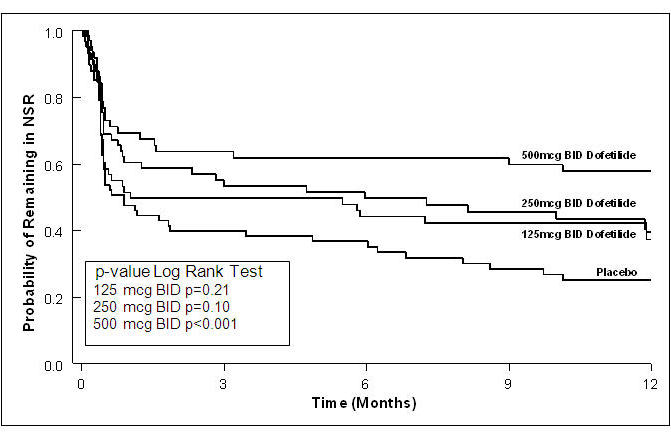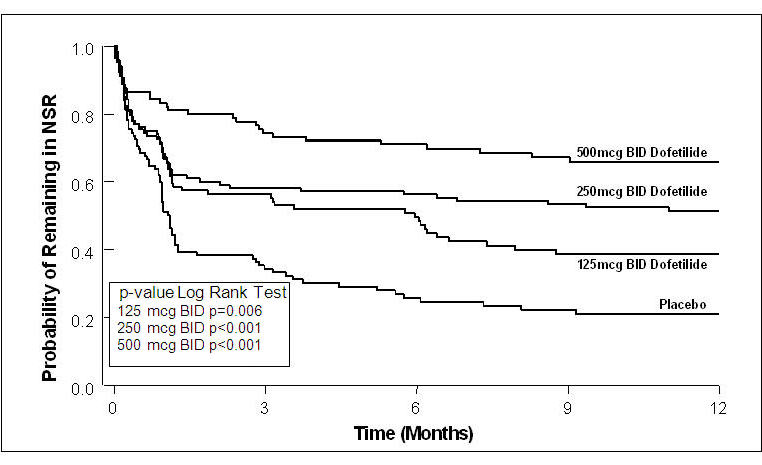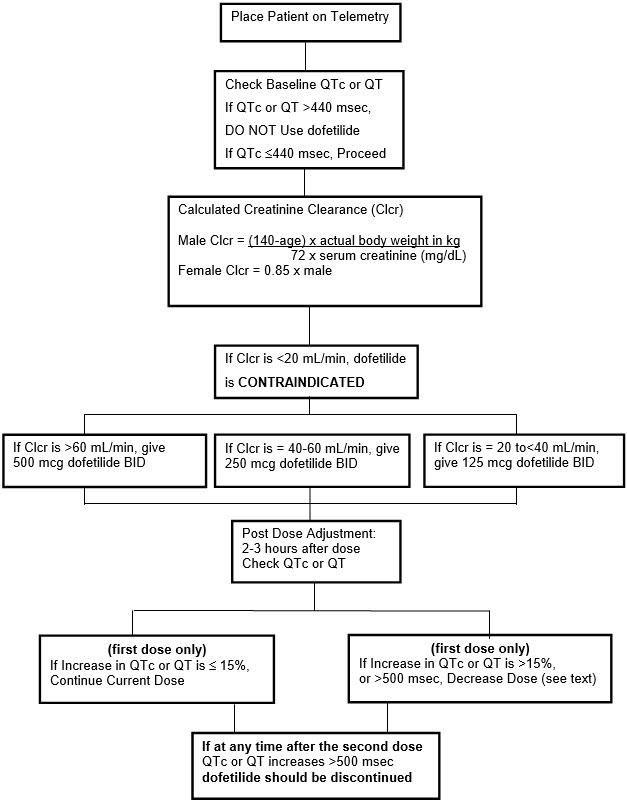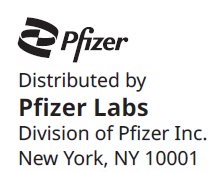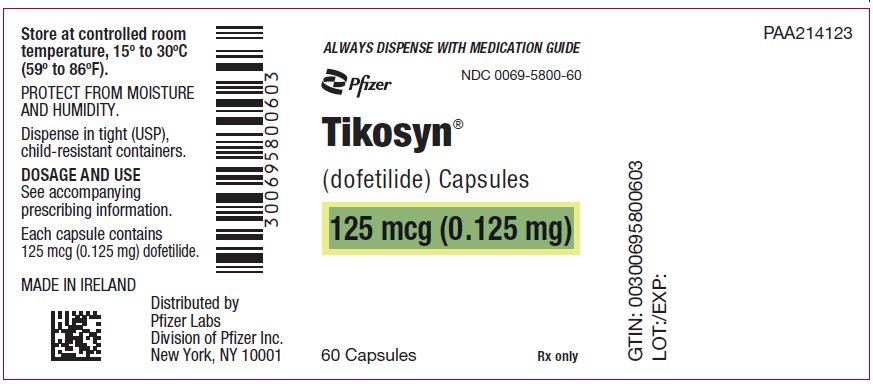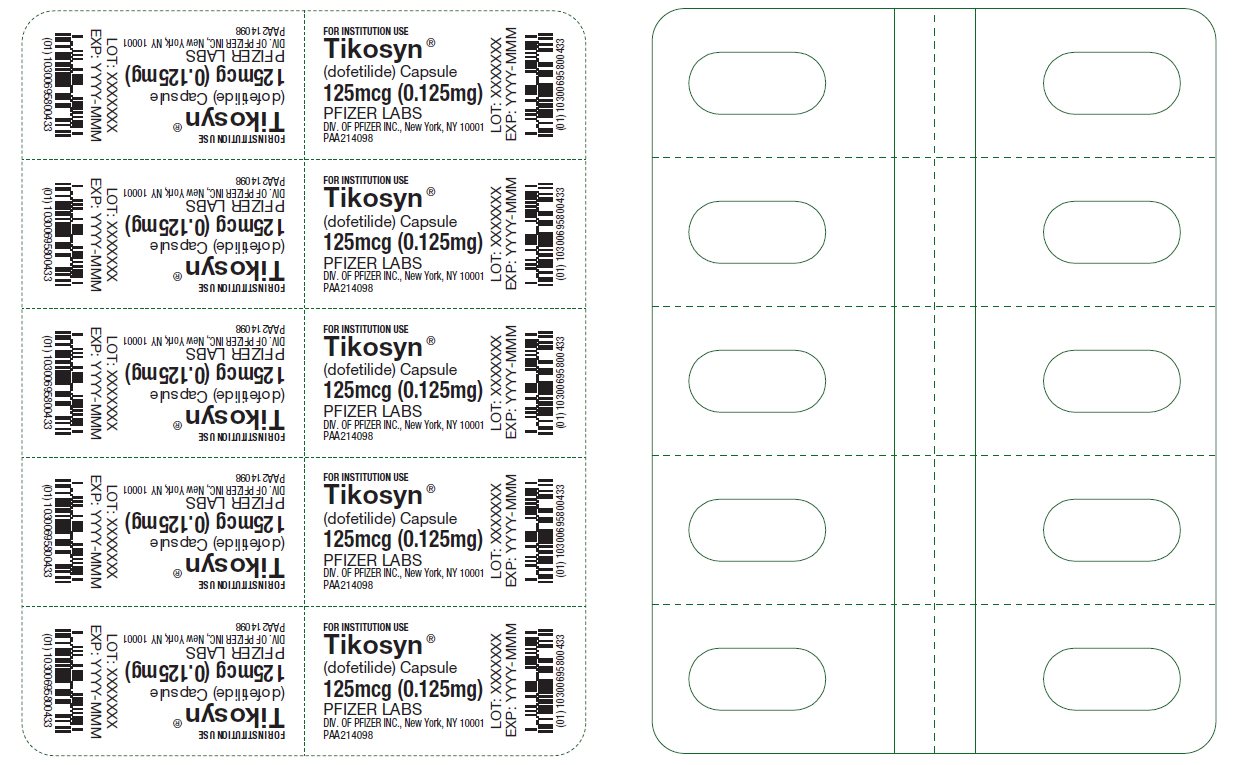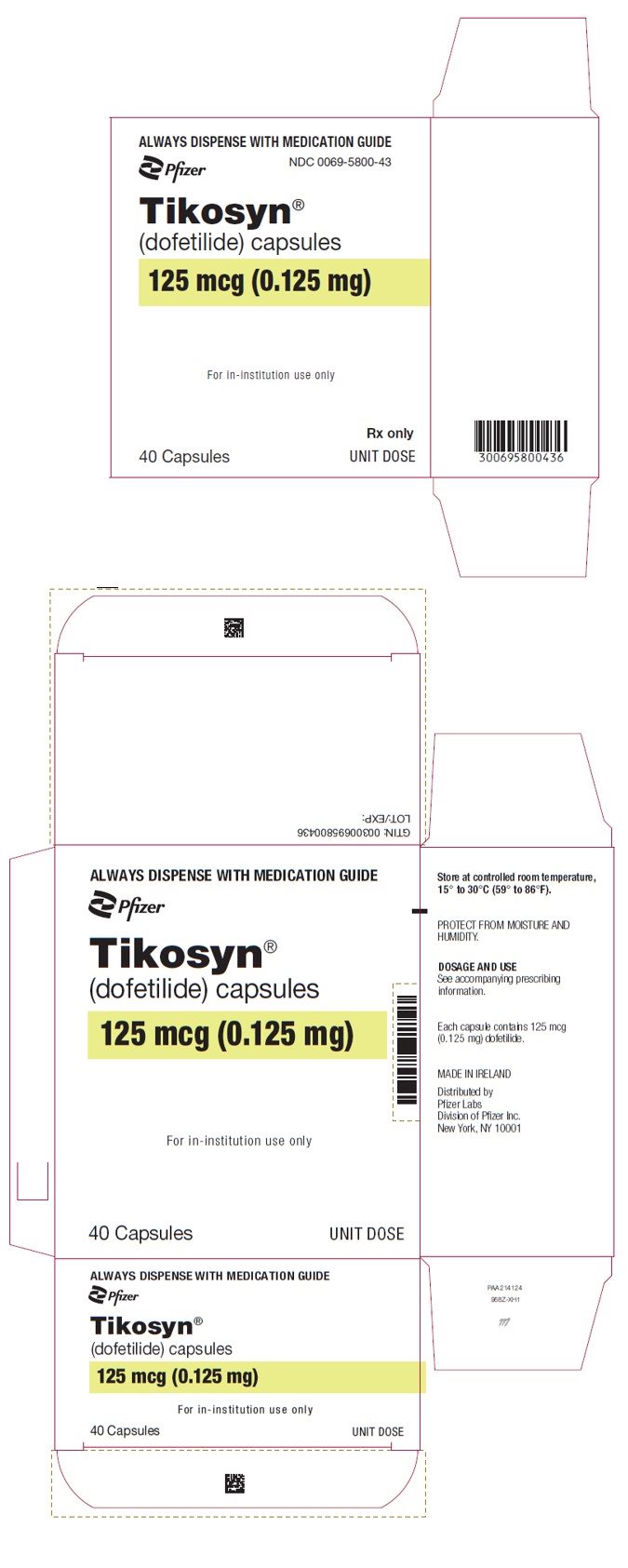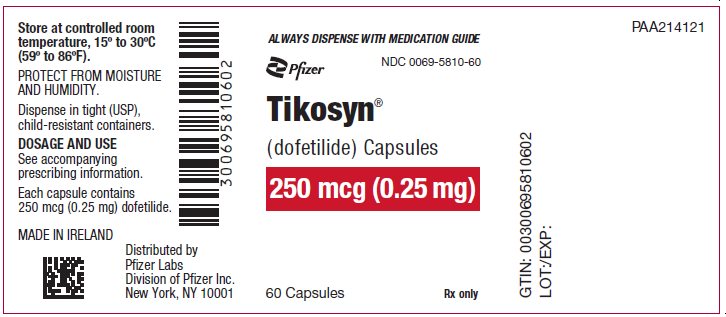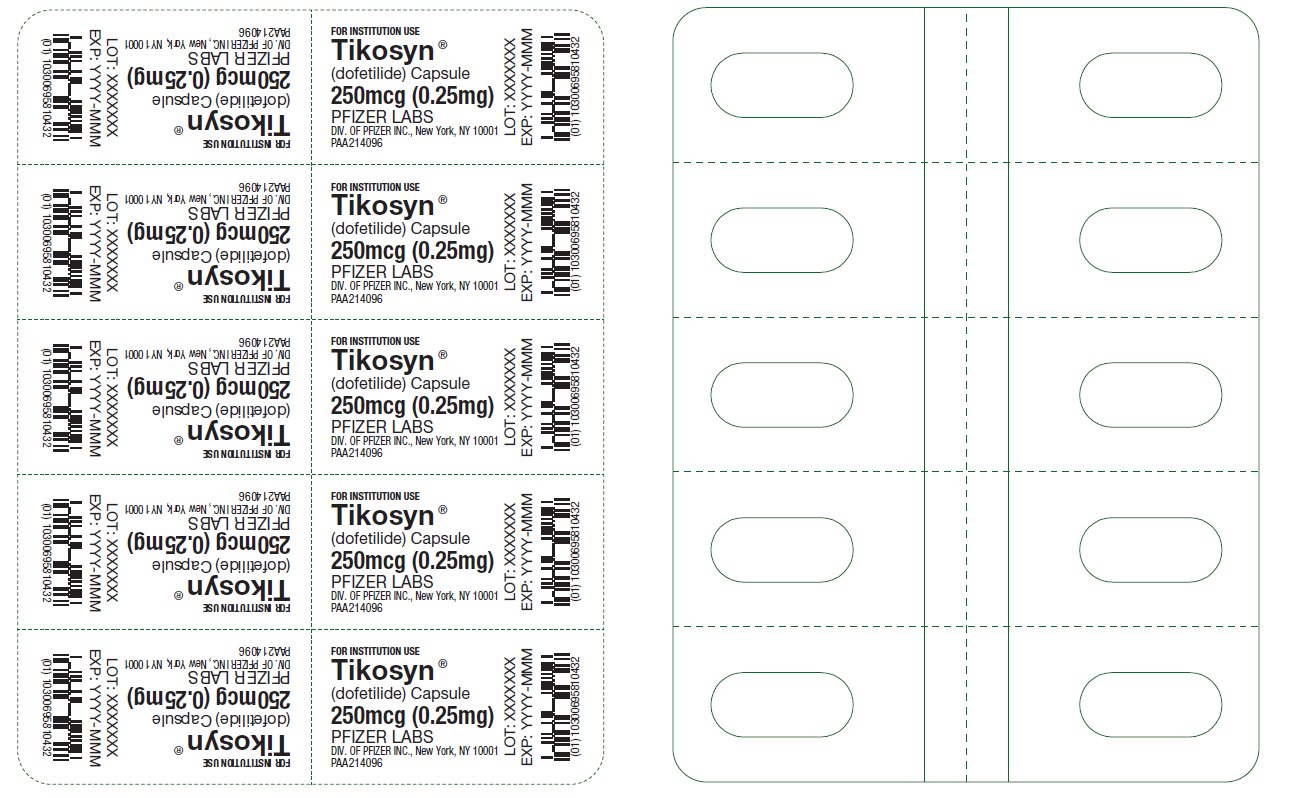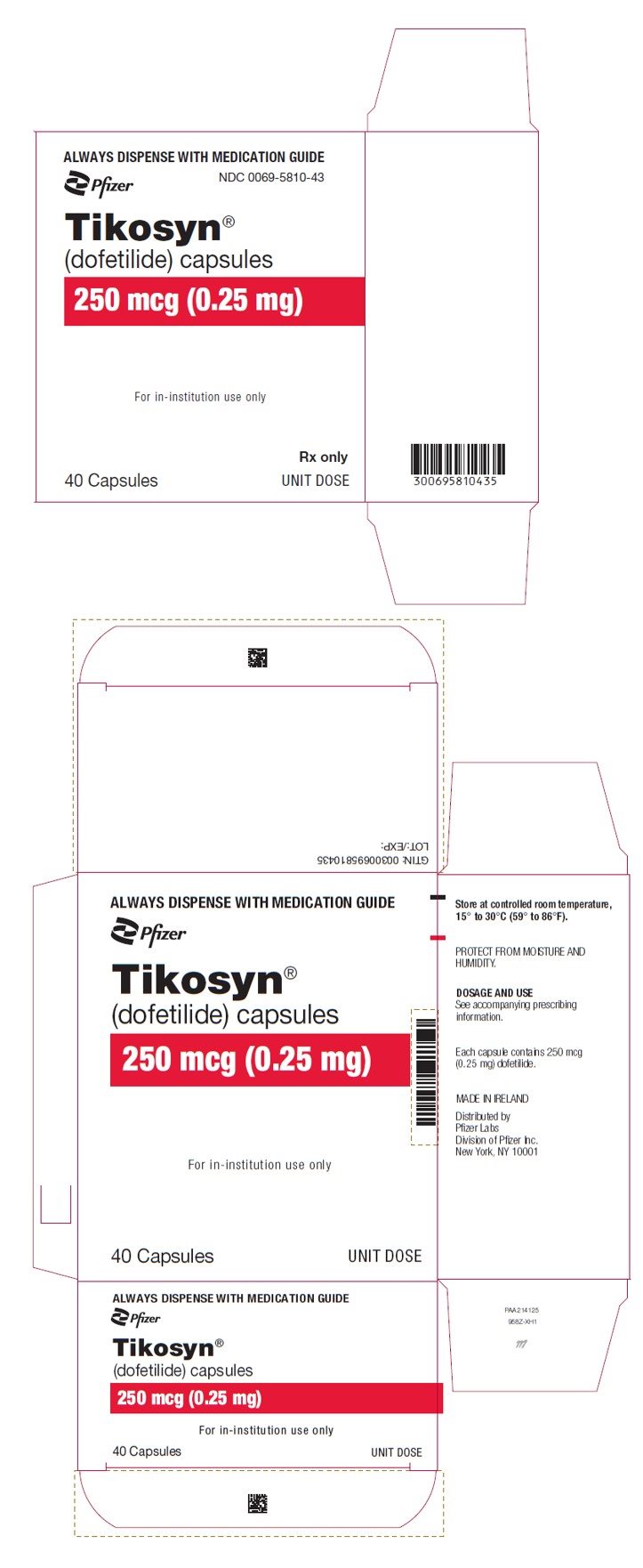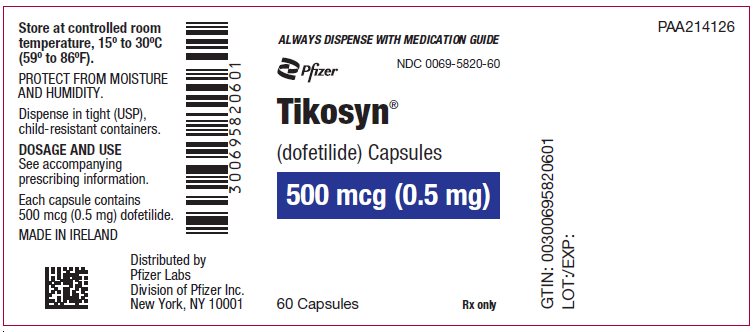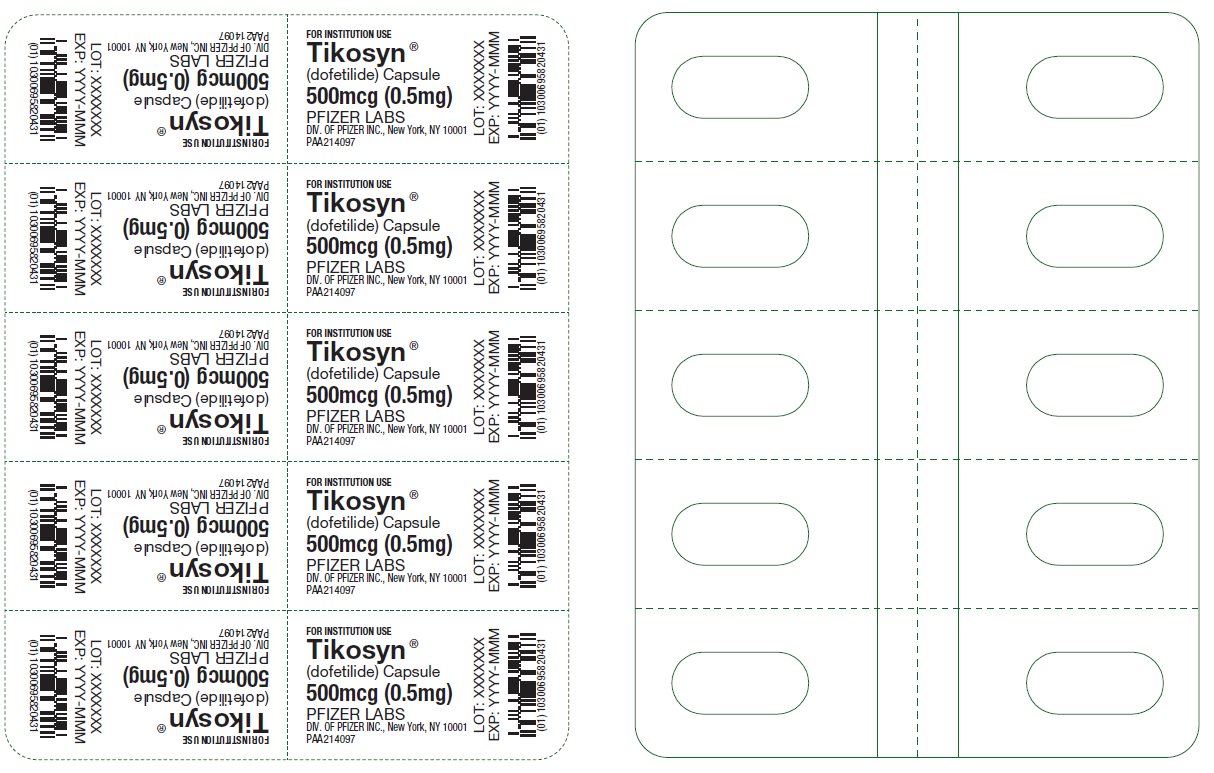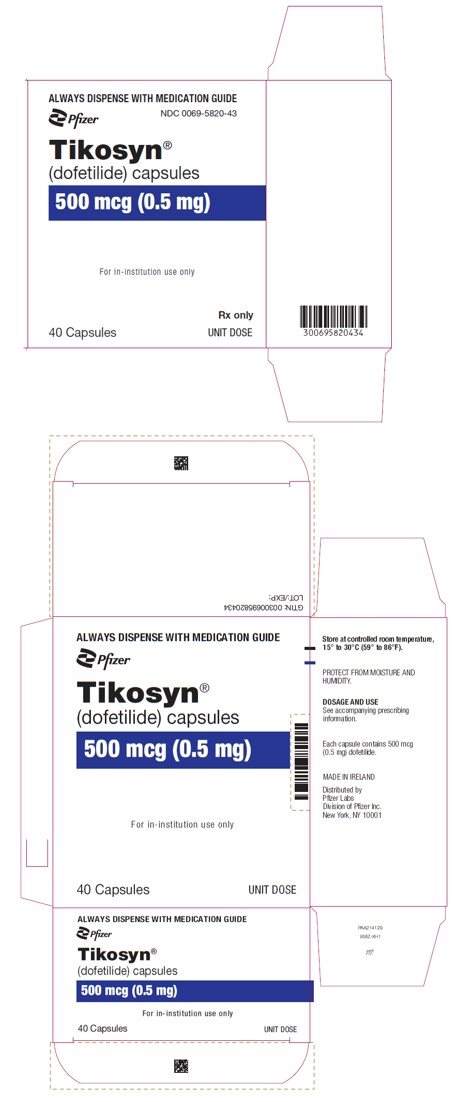 DRUG LABEL: Tikosyn
NDC: 0069-5800 | Form: CAPSULE
Manufacturer: Pfizer Laboratories Div Pfizer Inc
Category: prescription | Type: HUMAN PRESCRIPTION DRUG LABEL
Date: 20250209

ACTIVE INGREDIENTS: DOFETILIDE 0.125 mg/1 1
INACTIVE INGREDIENTS: MICROCRYSTALLINE CELLULOSE; STARCH, CORN; SILICON DIOXIDE; MAGNESIUM STEARATE

TIKOSYN ®
(dofetilide)
Capsules

BOXED WARNING

To minimize the risk of induced arrhythmia, patients initiated or re-initiated on TIKOSYN should be placed for a minimum of 3 days in a facility that can provide calculations of creatinine clearance, continuous electrocardiographic monitoring, and cardiac resuscitation. For detailed instructions regarding dose selection, see DOSAGE AND ADMINISTRATION.

DESCRIPTION

TIKOSYN® (dofetilide) is an antiarrhythmic drug with Class III (cardiac action potential duration prolonging) properties. Its empirical formula is C19H27N3O5S2 and it has a molecular weight of 441.6. The structural formula is

The chemical name for dofetilide is:
N-[4-[2-[methyl[2-[4-[(methylsulfonyl)amino]phenoxy]ethyl]amino]ethyl]phenyl]-methanesulfonamide.

Dofetilide is a white to off-white powder. It is very slightly soluble in water and propan-2-ol and is soluble in 0.1M aqueous sodium hydroxide, acetone, and aqueous 0.1M hydrochloric acid.

TIKOSYN capsules contain the following inactive ingredients: microcrystalline cellulose, corn starch, colloidal silicon dioxide and magnesium stearate. TIKOSYN is supplied for oral administration in three dosage strengths: 125 mcg (0.125 mg) orange and white capsules, 250 mcg (0.25 mg) peach capsules, and 500 mcg (0.5 mg) peach and white capsules.

CLINICAL PHARMACOLOGY

Mechanism of Action

Dofetilide shows Vaughan Williams Class III antiarrhythmic activity. The mechanism of action is blockade of the cardiac ion channel carrying the rapid component of the delayed rectifier potassium current, IKr. At concentrations covering several orders of magnitude, dofetilide blocks only IKr with no relevant block of the other repolarizing potassium currents (e.g., IKs, IK1). At clinically relevant concentrations, dofetilide has no effect on sodium channels (associated with Class I effect), adrenergic alpha-receptors, or adrenergic beta-receptors.

Electrophysiology

Dofetilide increases the monophasic action potential duration in a predictable, concentration-dependent manner, primarily due to delayed repolarization. This effect, and the related increase in effective refractory period, is observed in the atria and ventricles in both resting and paced electrophysiology studies. The increase in QT interval observed on the surface ECG is a result of prolongation of both effective and functional refractory periods in the His-Purkinje system and the ventricles.

Dofetilide did not influence cardiac conduction velocity and sinus node function in a variety of studies in patients with or without structural heart disease. This is consistent with a lack of effect of dofetilide on the PR interval and QRS width in patients with pre-existing heart block and/or sick sinus syndrome.

In patients, dofetilide terminates induced re-entrant tachyarrhythmias (e.g., atrial fibrillation/flutter and ventricular tachycardia) and prevents their re-induction. Dofetilide does not increase the electrical energy required to convert electrically induced ventricular fibrillation, and it significantly reduces the defibrillation threshold in patients with ventricular tachycardia and ventricular fibrillation undergoing implantation of a cardioverter-defibrillator device.

Hemodynamic Effects

In hemodynamic studies, dofetilide had no effect on cardiac output, cardiac index, stroke volume index, or systemic vascular resistance in patients with ventricular tachycardia, mild to moderate congestive heart failure or angina, and either normal or low left ventricular ejection fraction. There was no evidence of a negative inotropic effect related to dofetilide therapy in patients with atrial fibrillation. There was no increase in heart failure in patients with significant left ventricular dysfunction (see CLINICAL STUDIES, Safety in Patients with Structural Heart Disease, DIAMOND Studies). In the overall clinical program, dofetilide did not affect blood pressure. Heart rate was decreased by 4–6 bpm in studies in patients.

Pharmacokinetics, General

Absorption and Distribution: The oral bioavailability of dofetilide is >90%, with maximal plasma concentrations occurring at about 2–3 hours in the fasted state. Oral bioavailability is unaffected by food or antacid. The terminal half-life of dofetilide is approximately 10 hours; steady state plasma concentrations are attained within 2–3 days, with an accumulation index of 1.5 to 2.0. Plasma concentrations are dose proportional. Plasma protein binding of dofetilide is 60–70%, is independent of plasma concentration, and is unaffected by renal impairment. Volume of distribution is 3 L/kg.

Metabolism and Excretion:

Approximately 80% of a single dose of dofetilide is excreted in urine, of which approximately 80% is excreted as unchanged dofetilide with the remaining 20% consisting of inactive or minimally active metabolites. Renal elimination involves both glomerular filtration and active tubular secretion (via the cation transport system, a process that can be inhibited by cimetidine, trimethoprim, prochlorperazine, megestrol, ketoconazole and dolutegravir). In vitro studies with human liver microsomes show that dofetilide can be metabolized by CYP3A4, but it has a low affinity for this isoenzyme. Metabolites are formed by N-dealkylation and N-oxidation. There are no quantifiable metabolites circulating in plasma, but 5 metabolites have been identified in urine.

Pharmacokinetics in Special Populations

Renal Impairment:

In volunteers with varying degrees of renal impairment and patients with arrhythmias, the clearance of dofetilide decreases with decreasing creatinine clearance. As a result, and as seen in clinical studies, the half-life of dofetilide is longer in patients with lower creatinine clearances. Because increase in QT interval and the risk of ventricular arrhythmias are directly related to plasma concentrations of dofetilide, dosage adjustment based on calculated creatinine clearance is critically important (see DOSAGE AND ADMINISTRATION). Patients with severe renal impairment (creatinine clearance <20 mL/min) were not included in clinical or pharmacokinetic studies (see CONTRAINDICATIONS).

Hepatic Impairment:

There was no clinically significant alteration in the pharmacokinetics of dofetilide in volunteers with mild to moderate hepatic impairment (Child-Pugh Class A and B) compared to age- and weight-matched healthy volunteers. Patients with severe hepatic impairment were not studied.

Patients with Heart Disease:

Population pharmacokinetic analyses indicate that the plasma concentration of dofetilide in patients with supraventricular and ventricular arrhythmias, ischemic heart disease, or congestive heart failure are similar to those of healthy volunteers, after adjusting for renal function.

Elderly:

After correction for renal function, clearance of dofetilide is not related to age.

Women:

A population pharmacokinetic analysis showed that women have approximately 12–18% lower dofetilide oral clearances than men (14–22% greater plasma dofetilide levels), after correction for weight and creatinine clearance. In females, as in males, renal function was the single most important factor influencing dofetilide clearance. In normal female volunteers, hormone replacement therapy (a combination of conjugated estrogens and medroxyprogesterone) did not increase dofetilide exposure.

Drug-Drug Interactions

(see PRECAUTIONS)

Dose-Response and Concentration Response for Increase in QT Interval

Increase in QT interval is directly related to dofetilide dose and plasma concentration. Figure 1 shows that the relationship in normal volunteers between dofetilide plasma concentrations and change in QTc is linear, with a positive slope of approximately 15–25 msec/(ng/mL) after the first dose and approximately 10–15 msec/(ng/mL) at Day 23 (reflecting a steady state of dosing). A linear relationship between mean QTc increase and dofetilide dose was also seen in patients with renal impairment, in patients with ischemic heart disease, and in patients with supraventricular and ventricular arrhythmias.

Figure 1: Mean QTc-Concentration Relationship in Young Volunteers Over 24 Days

Note: The range of dofetilide plasma concentrations achieved with the 500 mcg BID dose adjusted for creatinine clearance is 1–3.5 ng/mL.

The relationship between dose, efficacy, and the increase in QTc from baseline at steady state for the two randomized, placebo-controlled studies (described further below) is shown in Figure 2. The studies examined the effectiveness of TIKOSYN in conversion to sinus rhythm and maintenance of normal sinus rhythm after conversion in patients with atrial fibrillation/flutter of >1 week duration. As shown, both the probability of a patient's remaining in sinus rhythm at six months and the change in QTc from baseline at steady state of dosing increased in an approximately linear fashion with increasing dose of TIKOSYN. Note that in these studies, doses were modified by results of creatinine clearance measurement and in-hospital QTc prolongation.

Figure 2: Relationship Between TIKOSYN Dose, QTc Increase and Maintenance of NSR
Number of patients evaluated for maintenance of NSR: 503 TIKOSYN, 174 placebo.
Number of patients evaluated for QTc change: 478 TIKOSYN, 167 placebo.

CLINICAL STUDIES

Chronic Atrial Fibrillation and/or Atrial Flutter

Two randomized, parallel, double-blind, placebo-controlled, dose-response trials evaluated the ability of TIKOSYN 1) to convert patients with atrial fibrillation or atrial flutter (AF/AFl) of more than 1 week duration to normal sinus rhythm (NSR) and 2) to maintain NSR (delay time to recurrence of AF/AFl) after drug-induced or electrical cardioversion. A total of 996 patients with a one week to two year history of atrial fibrillation/atrial flutter were enrolled. Both studies randomized patients to placebo or to doses of TIKOSYN 125 mcg, 250 mcg, 500 mcg, or in one study a comparator drug, given twice a day (these doses were lowered based on calculated creatinine clearance and, in one of the studies, for QT interval or QTc). All patients were started on therapy in a hospital where their ECG was monitored (see DOSAGE AND ADMINISTRATION).

Patients were excluded from participation if they had had syncope within the past 6 months, AV block greater than first degree, MI or unstable angina within 1 month, cardiac surgery within 2 months, history of QT interval prolongation or polymorphic ventricular tachycardia associated with use of antiarrhythmic drugs, QT interval or QTc >440 msec, serum creatinine >2.5 mg/mL, significant diseases of other organ systems; used cimetidine; or used drugs known to prolong the QT interval.

Both studies enrolled mostly Caucasians (over 90%), males (over 70%), and patients ≥65 years of age (over 50%). Most (>90%) were NYHA Functional Class I or II. Approximately one-half had structural heart disease (including ischemic heart disease, cardiomyopathies, and valvular disease) and about one-half were hypertensive. A substantial proportion of patients were on concomitant therapy, including digoxin (over 60%), diuretics (over 20%), and ACE inhibitors (over 30%). About 90% were on anticoagulants.

Acute conversion rates are shown in Table 1 for randomized doses (doses were adjusted for calculated creatinine clearance and, in Study 1, for QT interval or QTc). Of patients who converted pharmacologically, approximately 70% converted within 24–36 hours.

Table 1: Conversion of Atrial Fibrillation/Flutter to Normal Sinus Rhythm
 | TIKOSYN Dose |  |  | Placebo
 | 125 mcg BID | 250 mcg BID | 500 mcg BID | Placebo
Study 1 | 5/82(6%) | 8/82(10%) | 23/77(30%) | 1/84(1%)
Study 2 | 8/135(6%) | 14/133(11%) | 38/129(29%) | 2/137(1%)

Patients who did not convert to NSR with randomized therapy within 48–72 hours had electrical cardioversion. Those patients remaining in NSR after conversion in hospital were continued on randomized therapy as outpatients (maintenance period) for up to one year unless they experienced a recurrence of atrial fibrillation/atrial flutter or withdrew for other reasons.

Table 2 shows, by randomized dose, the percentage of patients at 6 and 12 months in both studies who remained on treatment in NSR and the percentage of patients who withdrew because of recurrence of AF/AFl or adverse events.

Table 2: Patient Status at 6 and 12 Months Post Randomization
 | TIKOSYN Dose |  |  | Placebo
 | 125 mcg BID | 250 mcg BID | 500 mcg BID | Placebo
Study 1
Randomized | 82 | 82 | 77 | 84
Achieved NSR | 60 | 61 | 61 | 68
6 months
Still on treatment in NSR | 38% | 44% | 52% | 32%
D/C for recurrence | 55% | 49% | 33% | 63%
D/C for AEs | 3% | 3% | 8% | 4%
12 months
Still on treatment in NSR | 32% | 26% | 46% | 22%
D/C for recurrence | 58% | 57% | 36% | 72%
D/C for AEs | 7% | 11% | 8% | 6%
Study 2
Randomized | 135 | 133 | 129 | 137
Achieved NSR | 103 | 118 | 100 | 106
6 months
Still on treatment in NSR | 41% | 49% | 57% | 22%
D/C for recurrence | 48% | 42% | 27% | 72%
D/C for AEs | 9% | 6% | 10% | 4%
12 months
Still on treatment in NSR | 25% | 42% | 49% | 16%
D/C for recurrence | 59% | 47% | 32% | 76%
D/C for AEs | 11% | 6% | 12% | 5%
Note that columns do not add up to 100% due to discontinuations for "other" reasons.

Table 3 and Figures 3 and 4 show, by randomized dose, the effectiveness of TIKOSYN in maintaining NSR using Kaplan Meier analysis, which shows patients remaining on treatment.

Table 3: P-Values and Median Time (days) to Recurrence of AF/AFl
 | TIKOSYN Dose |  |  | Placebo
 | 125 mcg BID | 250 mcg BID | 500 mcg BID | Placebo
Study 1
p-value vs. placebo | P=0.21 | P=0.10 | P<0.001
Median time to recurrence (days) | 31 | 179 | >365 | 27
Study 2
p-value vs. placebo | P=0.006 | P<0.001 | P<0.001
Median time to recurrence (days) | 182 | >365 | >365 | 34
Median time to recurrence of AF/AFl could not be estimated accurately for the 250 mcg BID treatment group in Study 2 and the 500 mcg BID treatment groups in Studies 1 and 2 because TIKOSYN maintained >50% of patients (51%, 58%, and 66%, respectively) in NSR for the 12 months duration of the studies.

Figure 3: Maintenance of Normal Sinus Rhythm, TIKOSYN Regimen vs. Placebo (Study 1)

The point estimates of the probabilities of remaining in NSR at 6 and 12 months were 62% and 58%, respectively, for TIKOSYN 500 mcg BID; 50% and 37%, respectively, for TIKOSYN 250 mcg BID; and 37%, and 25%, respectively, for placebo.

Figure 4: Maintenance of Normal Sinus Rhythm, TIKOSYN Regimen vs. Placebo (Study 2)

The point estimates of the probabilities of remaining in NSR at 6 and 12 months were 71% and 66%, respectively, for TIKOSYN 500 mcg BID; 56% and 51%, respectively, for TIKOSYN 250 mcg BID; and 26% and 21%, respectively, for placebo.

In both studies, TIKOSYN resulted in a dose-related increase in the number of patients maintained in NSR at all time periods and delayed the time of recurrence of sustained AF. Data pooled from both studies show that there is a positive relationship between the probability of staying in NSR, TIKOSYN dose, and increase in QTc (see Figure 2 in CLINICAL PHARMACOLOGY, Dose-Response and Concentration Response for Increase in QT Interval).

Analysis of pooled data for patients randomized to a TIKOSYN dose of 500 mcg twice daily showed that maintenance of NSR was similar in both males and females, in both patients aged <65 years and patients ≥65 years of age, and in both patients with atrial flutter as a primary diagnosis and those with a primary diagnosis of atrial fibrillation.

During the period of in-hospital initiation of dosing, 23% of patients in Studies 1 and 2 had their dose adjusted downward on the basis of their calculated creatinine clearance, and 3% had their dose down-titrated due to increased QT interval or QTc. Increased QT interval or QTc led to discontinuation of therapy in 3% of patients.

Safety in Patients with Structural Heart Disease: DIAMOND Studies (The Danish Investigations of Arrhythmia and Mortality on Dofetilide)

The two DIAMOND studies were 3-year trials comparing the effects of TIKOSYN and placebo on mortality and morbidity in patients with impaired left ventricular function (ejection fraction ≤35%). Patients were treated for at least one year. One study was in patients with moderate to severe (60% NYHA Class III or IV) congestive heart failure (DIAMOND CHF) and the other was in patients with recent myocardial infarction (DIAMOND MI) (of whom 40% had NYHA Class III or IV heart failure). Both groups were at relatively high risk of sudden death. The DIAMOND trials were intended to determine whether TIKOSYN could reduce that risk. The trials did not demonstrate a reduction in mortality; however, they provide reassurance that, when initiated carefully, in a hospital or equivalent setting, TIKOSYN did not increase mortality in patients with structural heart disease, an important finding because other antiarrhythmics [notably the Class IC antiarrhythmics studied in the Cardiac Arrhythmia Suppression Trial (CAST) and a pure Class III antiarrhythmic, d-sotalol (SWORD)] have increased mortality in post-infarction populations. The DIAMOND trials therefore provide evidence of a method of safe use of TIKOSYN in a population susceptible to ventricular arrhythmias. In addition, the subset of patients with AF in the DIAMOND trials provide further evidence of safety in a population of patients with structural heart disease accompanying the AF. Note, however, that this AF population was given a lower (250 mcg BID) dose (see CLINICAL STUDIES, DIAMOND Patients with Atrial Fibrillation).

In both DIAMOND studies, patients were randomized to 500 mcg BID of TIKOSYN, but this was reduced to 250 mcg BID if calculated creatinine clearance was 40–60 mL/min, if patients had AF, or if QT interval prolongation (>550 msec or >20% increase from baseline) occurred after dosing. Dose reductions for reduced calculated creatinine clearance occurred in 47% and 45% of DIAMOND CHF and MI patients, respectively. Dose reductions for increased QT interval or QTc occurred in 5% and 7% of DIAMOND CHF and MI patients, respectively. Increased QT interval or QTc (>550 msec or >20% increase from baseline) resulted in discontinuation of 1.8% of patients in DIAMOND CHF and 2.5% of patients in DIAMOND MI.

In the DIAMOND studies, all patients were hospitalized for at least 3 days after treatment was initiated and monitored by telemetry. Patients with QTc greater than 460 msec, second or third degree AV block (unless with pacemaker), resting heart rate <50 bpm, or prior history of polymorphic ventricular tachycardia were excluded.

DIAMOND CHF studied 1518 patients hospitalized with severe CHF who had confirmed impaired left ventricular function (ejection fraction ≤35%). Patients received a median duration of therapy of greater than one year. There were 311 deaths from all causes in patients randomized to TIKOSYN (n=762) and 317 deaths in patients randomized to placebo (n=756). The probability of survival at one year was 73% (95% CI: 70% – 76%) in the TIKOSYN group and 72% (95% CI: 69% – 75%) in the placebo group. Similar results were seen for cardiac deaths and arrhythmic deaths. Torsade de Pointes occurred in 25/762 patients (3.3%) receiving TIKOSYN. The majority of cases (76%) occurred within the first 3 days of dosing. In all, 437/762 (57%) of patients on TIKOSYN and 459/756 (61%) on placebo required hospitalization. Of these, 229/762 (30%) of patients on TIKOSYN and 290/756 (38%) on placebo required hospitalization because of worsening heart failure.

DIAMOND MI studied 1510 patients hospitalized with recent myocardial infarction (2–7 days) who had confirmed impaired left ventricular function (ejection fraction ≤35%). Patients received a median duration of therapy of greater than one year. There were 230 deaths in patients randomized to TIKOSYN (n=749) and 243 deaths in patients randomized to placebo (n=761). The probability of survival at one year was 79% (95% CI: 76% – 82%) in the TIKOSYN group and 77% (95% CI: 74% – 80%) in the placebo group. Cardiac and arrhythmic mortality showed a similar result. Torsade de Pointes occurred in 7/749 patients (0.9%) receiving TIKOSYN. Of these, 4 cases occurred within the first 3 days of dosing and 3 cases occurred between Day 4 and the conclusion of the study. In all, 371/749 (50%) of patients on TIKOSYN and 419/761 (55%) on placebo required hospitalization. Of these, 200/749 (27%) of patients on TIKOSYN and 205/761 (27%) on placebo required hospitalization because of worsening heart failure.

DIAMOND Patients with Atrial Fibrillation (the DIAMOND AF subpopulation). There were 506 patients in the two DIAMOND studies who had atrial fibrillation (AF) at entry to the studies (249 randomized to TIKOSYN and 257 randomized to placebo). DIAMOND AF patients randomized to TIKOSYN received 250 mcg BID; 65% of these patients had impaired renal function, so that 250 mcg BID represents the dose they would have received in the AF trials, which would give drug exposure similar to a person with normal renal function given 500 mcg BID. In the DIAMOND AF subpopulation, there were 111 deaths (45%) in the 249 patients in the TIKOSYN group and 116 deaths (45%) in the 257 patients in the placebo group. Hospital readmission rates for any reason were 125/249 or 50% on TIKOSYN and 156/257 or 61% for placebo. Of these, readmission rates for worsening heart failure were 73/249 or 29% on TIKOSYN and 102/257 or 40% for placebo.

Of the 506 patients in the DIAMOND studies who had atrial fibrillation or flutter at baseline, 12% of patients in the TIKOSYN group and 2% of patients in the placebo group had converted to normal sinus rhythm after one month. In those patients converted to normal sinus rhythm, 79% of the TIKOSYN group and 42% of the placebo group remained in normal sinus rhythm for one year.

In the DIAMOND studies, although Torsade de Pointes occurred more frequently in the TIKOSYN-treated patients (see ADVERSE REACTIONS), TIKOSYN, given with an initial 3-day hospitalization and with dose modified for reduced creatinine clearance and increased QT interval, was not associated with an excess risk of mortality in these populations with structural heart disease in the individual studies or in an analysis of the combined studies. The presence of atrial fibrillation did not affect outcome.

INDICATIONS AND USAGE

Maintenance of Normal Sinus Rhythm (Delay in AF/AFl Recurrence)

TIKOSYN is indicated for the maintenance of normal sinus rhythm (delay in time to recurrence of atrial fibrillation/atrial flutter [AF/AFl]) in patients with atrial fibrillation/atrial flutter of greater than one week duration who have been converted to normal sinus rhythm. Because TIKOSYN can cause life threatening ventricular arrhythmias, it should be reserved for patients in whom atrial fibrillation/atrial flutter is highly symptomatic.

In general, antiarrhythmic therapy for atrial fibrillation/atrial flutter aims to prolong the time in normal sinus rhythm. Recurrence is expected in some patients (see CLINICAL STUDIES).

Conversion of Atrial Fibrillation/Flutter

TIKOSYN is indicated for the conversion of atrial fibrillation and atrial flutter to normal sinus rhythm.

TIKOSYN has not been shown to be effective in patients with paroxysmal atrial fibrillation.

CONTRAINDICATIONS

TIKOSYN is contraindicated in patients with congenital or acquired long QT syndromes. TIKOSYN should not be used in patients with a baseline QT interval or QTc >440 msec (500 msec in patients with ventricular conduction abnormalities). TIKOSYN is also contraindicated in patients with severe renal impairment (calculated creatinine clearance <20 mL/min).

The concomitant use of verapamil or the cation transport system inhibitors cimetidine, trimethoprim (alone or in combination with sulfamethoxazole), or ketoconazole with TIKOSYN is contraindicated (see WARNINGS and PRECAUTIONS, Drug-Drug Interactions), as each of these drugs cause a substantial increase in dofetilide plasma concentrations. In addition, other known inhibitors of the renal cation transport system such as prochlorperazine, dolutegravir and megestrol should not be used in patients on TIKOSYN.

The concomitant use of hydrochlorothiazide (alone or in combinations such as with triamterene) with TIKOSYN is contraindicated (see PRECAUTIONS, Drug-Drug Interactions) because this has been shown to significantly increase dofetilide plasma concentrations and QT interval prolongation.

TIKOSYN is also contraindicated in patients with a known hypersensitivity to the drug.

WARNINGS

Ventricular Arrhythmia:

TIKOSYN (dofetilide) can cause serious ventricular arrhythmias, primarily Torsade de Pointes (TdP) type ventricular tachycardia, a polymorphic ventricular tachycardia associated with QT interval prolongation. QT interval prolongation is directly related to dofetilide plasma concentration. Factors such as reduced creatinine clearance or certain dofetilide drug interactions will increase dofetilide plasma concentration. The risk of TdP can be reduced by controlling the plasma concentration through adjustment of the initial dofetilide dose according to creatinine clearance and by monitoring the ECG for excessive increases in the QT interval.

Treatment with dofetilide must therefore be started only in patients placed for a minimum of three days in a facility that can provide electrocardiographic monitoring and in the presence of personnel trained in the management of serious ventricular arrhythmias. Calculation of the creatinine clearance for all patients must precede administration of the first dose of dofetilide. For detailed instructions regarding dose selection, see DOSAGE AND ADMINISTRATION.

The risk of dofetilide induced ventricular arrhythmia was assessed in three ways in clinical studies: 1) by description of the QT interval and its relation to the dose and plasma concentration of dofetilide; 2) by observing the frequency of TdP in TIKOSYN-treated patients according to dose; 3) by observing the overall mortality rate in patients with atrial fibrillation and in patients with structural heart disease.

Relation of QT Interval to Dose:

The QT interval increases linearly with increasing TIKOSYN dose (see Figures 1 and 2 in CLINICAL PHARMACOLOGY and Dose-Response and Concentration Response for Increase in QT Interval).

Frequency of Torsade de Pointes:

In the supraventricular arrhythmia population (patients with AF and other supraventricular arrhythmias), the overall incidence of Torsade de Pointes was 0.8%. The frequency of TdP by dose is shown in Table 4. There were no cases of TdP on placebo.

Table 4: Summary of Torsade de Pointes in Patients Randomized to Dofetilide by Dose; Patients with Supraventricular Arrhythmias
 | TIKOSYN Dose
 | <250 mcg BID | 250 mcg BID | >250–500 mcg BID | >500 mcg BID | All Doses
Number of Patients | 217 | 388 | 703 | 38 | 1346
Torsade de Pointes | 0 | 1 (0.3%) | 6 (0.9%) | 4 (10.5%) | 11 (0.8%)

As shown in Table 5, the rate of TdP was reduced when patients were dosed according to their renal function (see CLINICAL PHARMACOLOGY, Pharmacokinetics in Special Populations, Renal Impairment and DOSAGE AND ADMINISTRATION).

Table 5: Incidence of Torsade de Pointes Before and After Introduction of Dosing According to Renal Function
Population: | Total | Before | After
Population: | n/N % | n/N % | n/N %
Supraventricular Arrhythmias | 11/1346 (0.8%) | 6/193 (3.1%) | 5/1153 (0.4%)
DIAMOND CHF | 25/762 (3.3%) | 7/148 (4.7%) | 18/614 (2.9%)
DIAMOND MI | 7/749 (0.9%) | 3/101 (3.0%) | 4/648 (0.6%)
DIAMOND AF | 4/249 (1.6%) | 0/43 (0%) | 4/206 (1.9%)

The majority of the episodes of TdP occurred within the first three days of TIKOSYN therapy (10/11 events in the studies of patients with supraventricular arrhythmias; 19/25 and 4/7 events in DIAMOND CHF and DIAMOND MI, respectively; 2/4 events in the DIAMOND AF subpopulation).

Mortality:

In a pooled survival analysis of patients in the supraventricular arrhythmia population (low prevalence of structural heart disease), deaths occurred in 0.9% (12/1346) of patients receiving TIKOSYN and 0.4% (3/677) in the placebo group. Adjusted for duration of therapy, primary diagnosis, age, gender, and prevalence of structural heart disease, the point estimate of the hazard ratio for the pooled studies (TIKOSYN/placebo) was 1.1 (95% CI: 0.3, 4.3). The DIAMOND CHF and MI trials examined mortality in patients with structural heart disease (ejection fraction ≤35%). In these large, double-blind studies, deaths occurred in 36% (541/1511) of TIKOSYN patients and 37% (560/1517) of placebo patients. In an analysis of 506 DIAMOND patients with atrial fibrillation/flutter at baseline, one year mortality on TIKOSYN was 31% vs. 32% on placebo (see CLINICAL STUDIES).

Because of the small number of events, an excess mortality due to TIKOSYN cannot be ruled out with confidence in the pooled survival analysis of placebo-controlled trials in patients with supraventricular arrhythmias. However, it is reassuring that in two large placebo-controlled mortality studies in patients with significant heart disease (DIAMOND CHF/MI), there were no more deaths in TIKOSYN-treated patients than in patients given placebo (see CLINICAL STUDIES).

Drug-Drug Interactions

(see CONTRAINDICATIONS)

Because there is a linear relationship between dofetilide plasma concentration and QTc, concomitant drugs that interfere with the metabolism or renal elimination of dofetilide may increase the risk of arrhythmia (Torsade de Pointes). Dofetilide is metabolized to a small degree by the CYP3A4 isoenzyme of the cytochrome P450 system and an inhibitor of this system could increase systemic dofetilide exposure. More important, dofetilide is eliminated by cationic renal secretion, and three inhibitors of this process have been shown to increase systemic dofetilide exposure. The magnitude of the effect on renal elimination by cimetidine, trimethoprim, and ketoconazole (all contraindicated concomitant uses with dofetilide) suggests that all renal cation transport inhibitors should be contraindicated.

Hypokalemia and Potassium-Depleting Diuretics

Hypokalemia or hypomagnesemia may occur with administration of potassium-depleting diuretics, increasing the potential for Torsade de Pointes. Potassium levels should be within the normal range prior to administration of TIKOSYN and maintained in the normal range during administration of TIKOSYN (see DOSAGE AND ADMINISTRATION).

Use with Drugs that Prolong QT Interval and Antiarrhythmic Agents

The use of TIKOSYN in conjunction with other drugs that prolong the QT interval has not been studied and is not recommended. Such drugs include phenothiazines, cisapride, bepridil, tricyclic antidepressants, certain oral macrolides, and certain fluoroquinolones. Class I or Class III antiarrhythmic agents should be withheld for at least three half-lives prior to dosing with TIKOSYN. In clinical trials, TIKOSYN was administered to patients previously treated with oral amiodarone only if serum amiodarone levels were below 0.3 mg/L or amiodarone had been withdrawn for at least three months.

PRECAUTIONS

Renal Impairment

The overall systemic clearance of dofetilide is decreased and plasma concentration increased with decreasing creatinine clearance. The dose of TIKOSYN must be adjusted based on creatinine clearance (see DOSAGE AND ADMINISTRATION). Patients undergoing dialysis were not included in clinical studies, and appropriate dosing recommendations for these patients are unknown. There is no information about the effectiveness of hemodialysis in removing dofetilide from plasma.

Hepatic Impairment

After adjustment for creatinine clearance, no additional dose adjustment is required for patients with mild or moderate hepatic impairment. Patients with severe hepatic impairment have not been studied. TIKOSYN should be used with particular caution in these patients.

Cardiac Conduction Disturbances

Animal and human studies have not shown any adverse effects of dofetilide on conduction velocity. No effect on AV nodal conduction following TIKOSYN treatment was noted in normal volunteers and in patients with 1st degree heart block. Patients with sick sinus syndrome or with 2nd or 3rd degree heart block were not included in the Phase 3 clinical trials unless a functioning pacemaker was present. TIKOSYN has been used safely in conjunction with pacemakers (53 patients in DIAMOND studies, 136 in trials in patients with ventricular and supraventricular arrhythmias).

Information for Patients

Please refer patient to the Medication Guide.

Prior to initiation of TIKOSYN therapy, the patient should be advised to read the Medication Guide and reread it each time therapy is renewed in case the patient's status has changed. The patient should be fully instructed on the need for compliance with the recommended dosing of TIKOSYN and the potential for drug interactions, and the need for periodic monitoring of QTc and renal function to minimize the risk of serious abnormal rhythms.

Medications and Supplements:

Assessment of patients' medication history should include all over-the-counter, prescription, and herbal/natural preparations with emphasis on preparations that may affect the pharmacokinetics of TIKOSYN such as cimetidine (see CONTRAINDICATIONS), trimethoprim alone or in combination with sulfamethoxazole (see WARNINGS, CONTRAINDICATIONS), prochlorperazine (see WARNINGS, CONTRAINDICATIONS), megestrol (see WARNINGS, CONTRAINDICATIONS), ketoconazole (see WARNINGS, CONTRAINDICATIONS), dolutegravir (see CONTRAINDICATIONS), hydrochlorothiazide (alone or in combinations such as with triamterene) (see CONTRAINDICATIONS), other cardiovascular drugs (especially verapamil – see CONTRAINDICATIONS), phenothiazines, and tricyclic antidepressants (see WARNINGS). If a patient is taking TIKOSYN and requires anti-ulcer therapy, omeprazole, ranitidine, or antacids (aluminum and magnesium hydroxides) should be used as alternatives to cimetidine, as these agents have no effect on the pharmacokinetics of TIKOSYN. Patients should be instructed to notify their health care providers of any change in over-the-counter, prescription, or supplement use. If a patient is hospitalized or is prescribed a new medication for any condition, the patient must inform the health care provider of ongoing TIKOSYN therapy. Patients should also check with their health care provider and/or pharmacist prior to taking a new over-the-counter preparation.

Electrolyte Imbalance:

If patients experience symptoms that may be associated with altered electrolyte balance, such as excessive or prolonged diarrhea, sweating, or vomiting or loss of appetite or thirst, these conditions should immediately be reported to their health care provider.

Dosing Schedule:

Patients should be instructed NOT to double the next dose if a dose is missed. The next dose should be taken at the usual time.

Drug/Laboratory Test Interactions

None known.

Drug-Drug Interactions

Cimetidine:

(see WARNINGS, CONTRAINDICATIONS) Concomitant use of cimetidine is contraindicated. Cimetidine at 400 mg BID (the usual prescription dose) co-administered with TIKOSYN (500 mcg BID) for 7 days has been shown to increase dofetilide plasma levels by 58%. Cimetidine at doses of 100 mg BID (OTC dose) resulted in a 13% increase in dofetilide plasma levels (500 mcg single dose). No studies have been conducted at intermediate doses of cimetidine. If a patient requires TIKOSYN and anti-ulcer therapy, it is suggested that omeprazole, ranitidine, or antacids (aluminum and magnesium hydroxides) be used as alternatives to cimetidine, as these agents have no effect on the pharmacokinetic profile of TIKOSYN.

Verapamil:

(see CONTRAINDICATIONS) Concomitant use of verapamil is contraindicated. Co-administration of TIKOSYN with verapamil resulted in increases in dofetilide peak plasma levels of 42%, although overall exposure to dofetilide was not significantly increased. In an analysis of the supraventricular arrhythmia and DIAMOND patient populations, the concomitant administration of verapamil with dofetilide was associated with a higher occurrence of Torsade de Pointes.

Ketoconazole:

(see WARNINGS, CONTRAINDICATIONS) Concomitant use of ketoconazole is contraindicated. Ketoconazole at 400 mg daily (the maximum approved prescription dose) co-administered with TIKOSYN (500 mcg BID) for 7 days has been shown to increase dofetilide Cmax by 53% in males and 97% in females, and AUC by 41% in males and 69% in females.

Trimethoprim Alone or in Combination with Sulfamethoxazole:

(see WARNINGS, CONTRAINDICATIONS) Concomitant use of trimethoprim alone or in combination with sulfamethoxazole is contraindicated. Trimethoprim 160 mg in combination with 800 mg sulfamethoxazole co-administered BID with TIKOSYN (500 mcg BID) for 4 days has been shown to increase dofetilide AUC by 103% and Cmax by 93%.

Hydrochlorothiazide (HCTZ) Alone or in Combination with Triamterene:

(see CONTRAINDICATIONS) Concomitant use of HCTZ alone or in combination with triamterene is contraindicated. HCTZ 50 mg QD or HCTZ/triamterene 50/100 mg QD was co-administered with TIKOSYN (500 mcg BID) for 5 days (following 2 days of diuretic use at half dose). In patients receiving HCTZ alone, dofetilide AUC increased by 27% and Cmax by 21%. However, the pharmacodynamic effect increased by 197% (QTc increase over time) and by 95% (maximum QTc increase). In patients receiving HCTZ in combination with triamterene, dofetilide AUC increased by 30% and Cmax by 16%. However, the pharmacodynamic effect increased by 190% (QTc increase over time) and by 84% (maximum QTc increase). The pharmacodynamic effects can be explained by a combination of the increase in dofetilide exposure and the reductions in serum potassium. In the DIAMOND trials, 1252 patients were treated with TIKOSYN and diuretics concomitantly, of whom 493 died compared to 508 deaths among the 1248 patients receiving placebo and diuretics. Of the 229 patients who had potassium depleting diuretics added to their concomitant medications in the DIAMOND trials, the patients on TIKOSYN had a non-significantly reduced relative risk for death of 0.68 (95% CI: 0.376, 1.230).

Potential Drug Interactions

Dofetilide is eliminated in the kidney by cationic secretion. Inhibitors of renal cationic secretion are contraindicated with TIKOSYN. In addition, drugs that are actively secreted via this route (e.g., triamterene, metformin, and amiloride) should be co-administered with care as they might increase dofetilide levels.

Dofetilide is metabolized to a small extent by the CYP3A4 isoenzyme of the cytochrome P450 system. Inhibitors of the CYP3A4 isoenzyme could increase systemic dofetilide exposure. Inhibitors of this isoenzyme (e.g., macrolide antibiotics, azole antifungal agents, protease inhibitors, serotonin reuptake inhibitors, amiodarone, cannabinoids, diltiazem, grapefruit juice, nefazadone, norfloxacin, quinine, zafirlukast) should be cautiously co-administered with TIKOSYN as they can potentially increase dofetilide levels. Dofetilide is not an inhibitor of CYP3A4 nor of other cytochrome P450 isoenzymes (e.g., CYP2C9, CYP2D6) and is not expected to increase levels of drugs metabolized by CYP3A4.

Other Drug Interaction Information

Digoxin:

Studies in healthy volunteers have shown that TIKOSYN does not affect the pharmacokinetics of digoxin. In patients, the concomitant administration of digoxin with dofetilide was associated with a higher occurrence of Torsade de Pointes. It is not clear whether this represents an interaction with TIKOSYN or the presence of more severe structural heart disease in patients on digoxin; structural heart disease is a known risk factor for arrhythmia. No increase in mortality was observed in patients taking digoxin as concomitant medication.

Other Drugs:

In healthy volunteers, amlodipine, phenytoin, glyburide, ranitidine, omeprazole, hormone replacement therapy (a combination of conjugated estrogens and medroxyprogesterone), antacid (aluminum and magnesium hydroxides), and theophylline did not affect the pharmacokinetics of TIKOSYN. In addition, studies in healthy volunteers have shown that TIKOSYN does not affect the pharmacokinetics or pharmacodynamics of warfarin, or the pharmacokinetics of propranolol (40 mg twice daily), phenytoin, theophylline, or oral contraceptives.

Population pharmacokinetic analyses were conducted on plasma concentration data from 1445 patients in clinical trials to examine the effects of concomitant medications on clearance or volume of distribution of dofetilide. Concomitant medications were grouped as ACE inhibitors, oral anticoagulants, calcium channel blockers, beta blockers, cardiac glycosides, inducers of CYP3A4, substrates and inhibitors of CYP3A4, substrates and inhibitors of P-glycoprotein, nitrates, sulphonylureas, loop diuretics, potassium sparing diuretics, thiazide diuretics, substrates and inhibitors of tubular organic cation transport, and QTc-prolonging drugs. Differences in clearance between patients on these medications (at any occasion in the study) and those off medications varied between -16% and +3%. The mean clearances of dofetilide were 16% and 15% lower in patients on thiazide diuretics and inhibitors of tubular organic cation transport, respectively.

Carcinogenesis, Mutagenesis, Impairment of Fertility

Dofetilide had no genotoxic effects, with or without metabolic activation, based on the bacterial mutation assay and tests of cytogenetic aberrations in vivo in mouse bone marrow and in vitro in human lymphocytes. Rats and mice treated with dofetilide in the diet for two years showed no evidence of an increased incidence of tumors compared to controls. The highest dofetilide dose administered for 24 months was 10 mg/kg/day to rats and 20 mg/kg/day to mice. Mean dofetilide AUCs(0–24hr) at these doses were about 26 and 10 times, respectively, the maximum likely human AUC.

There was no effect on mating or fertility when dofetilide was administered to male and female rats at doses as high as 1.0 mg/kg/day, a dose that would be expected to provide a mean dofetilide AUC(0–24hr) about 3 times the maximum likely human AUC. Increased incidences of testicular atrophy and epididymal oligospermia and a reduction in testicular weight were, however, observed in other studies in rats. Reduced testicular weight and increased incidence of testicular atrophy were also consistent findings in dogs and mice. The no effect doses for these findings in chronic administration studies in these 3 species (3, 0.1, and 6 mg/kg/day) were associated with mean dofetilide AUCs that were about 4, 1.3, and 3 times the maximum likely human AUC, respectively.

Pregnancy

Dofetilide has been shown to adversely affect in utero growth and survival of rats and mice when orally administered during organogenesis at doses of 2 or more mg/kg/day. Other than an increased incidence of non-ossified 5th metacarpal, and the occurrence of hydroureter and hydronephroses at doses as low as 1 mg/kg/day in the rat, structural anomalies associated with drug treatment were not observed in either species at doses below 2 mg/kg/day. The clearest drug-effect associations were for sternebral and vertebral anomalies in both species; cleft palate, adactyly, levocardia, dilation of cerebral ventricles, hydroureter, hydronephroses, and unossified metacarpal in the rat; and increased incidence of unossified calcaneum in the mouse. The "no observed adverse effect dose" in both species was 0.5 mg/kg/day. The mean dofetilide AUCs(0–24hr) at this dose in the rat and mouse are estimated to be about equal to the maximum likely human AUC and about half the likely human AUC, respectively. There are no adequate and well controlled studies in pregnant women. Therefore, dofetilide should only be administered to pregnant women where the benefit to the patient justifies the potential risk to the fetus.

Nursing Mothers

There is no information on the presence of dofetilide in breast milk. Patients should be advised not to breast-feed an infant if they are taking TIKOSYN.

Geriatric Use

Of the total number of patients in clinical studies of TIKOSYN, 46% were 65 to 89 years old. No overall differences in safety, effect on QTc, or effectiveness were observed between elderly and younger patients. Because elderly patients are more likely to have decreased renal function with a reduced creatinine clearance, care must be taken in dose selection (see DOSAGE AND ADMINISTRATION).

Use in Women

Female patients constituted 32% of the patients in the placebo-controlled trials of TIKOSYN. As with other drugs that cause Torsade de Pointes, TIKOSYN was associated with a greater risk of Torsade de Pointes in female patients than in male patients. During the TIKOSYN clinical development program, the risk of Torsade de Pointes in females was approximately 3 times the risk in males. Unlike Torsade de Pointes, the incidence of other ventricular arrhythmias was similar in female patients receiving TIKOSYN and patients receiving placebo. Although no study specifically investigated this risk, in post-hoc analyses, no increased mortality was observed in females on TIKOSYN compared to females on placebo.

Pediatric Use

The safety and effectiveness of TIKOSYN in children (<18 years old) has not been established.

ADVERSE REACTIONS

The TIKOSYN clinical program involved approximately 8,600 patients in 130 clinical studies of normal volunteers and patients with supraventricular and ventricular arrhythmias. TIKOSYN was administered to 5,194 patients, including two large, placebo-controlled mortality trials (DIAMOND CHF and DIAMOND MI) in which 1,511 patients received TIKOSYN for up to three years.

In the following section, adverse reaction data for cardiac arrhythmias and non-cardiac adverse reactions are presented separately for patients included in the supraventricular arrhythmia development program and for patients included in the DIAMOND CHF and MI mortality trials (see CLINICAL STUDIES, Safety in Patients with Structural Heart Disease, DIAMOND Studies, for a description of these trials).

In studies of patients with supraventricular arrhythmias, a total of 1,346 and 677 patients were exposed to TIKOSYN and placebo for 551 and 207 patient years, respectively. A total of 8.7% of patients in the dofetilide groups were discontinued from clinical trials due to adverse events compared to 8.0% in the placebo groups. The most frequent reason for discontinuation (>1%) was ventricular tachycardia (2.0% on dofetilide vs. 1.3% on placebo). The most frequent adverse events were headache, chest pain, and dizziness.

Serious Arrhythmias and Conduction Disturbances:

Torsade de Pointes is the only arrhythmia that showed a dose-response relationship to TIKOSYN treatment. It did not occur in placebo treated patients. The incidence of Torsade de Pointes in patients with supraventricular arrhythmias was 0.8% (11/1346) (see WARNINGS). The incidence of Torsade de Pointes in patients who were dosed according to the recommended dosing regimen (see DOSAGE AND ADMINISTRATION) was 0.8% (4/525). Table 6 shows the frequency by randomized dose of serious arrhythmias and conduction disturbances reported as adverse events in patients with supraventricular arrhythmias.

Table 6: Incidence of Serious Arrhythmias and Conduction Disturbances in Patients with Supraventricular Arrhythmias
 | TIKOSYN Dose |  |  |  | Placebo
Arrhythmia event: | <250 mcg BID N=217 | 250 mcg BID N=388 | >250–500 mcg BID N=703 | >500 mcg BID N=38 | N=677
Ventricular arrhythmias [Patients with more than one arrhythmia are counted only once in this category.] [Ventricular arrhythmias and ventricular tachycardia include all cases of Torsade de Pointes.] | 3.7% | 2.6% | 3.4% | 15.8% | 2.7%
Ventricular fibrillation | 0 | 0.3% | 0.4% | 2.6% | 0.1%
Ventricular tachycardia | 3.7% | 2.6% | 3.3% | 13.2% | 2.5%
Torsade de Pointes | 0 | 0.3% | 0.9% | 10.5% | 0
Various forms of block
AV block | 0.9% | 1.5% | 0.4% | 0 | 0.3%
Bundle branch block | 0 | 0.5% | 0.1% | 0 | 0.1%
Heart block | 0 | 0.5% | 0.1% | 0 | 0.1%

In the DIAMOND trials, a total of 1,511 patients were exposed to TIKOSYN for 1757 patient years. The incidence of Torsade de Pointes was 3.3% in CHF patients and 0.9% in patients with a recent MI.

Table 7 shows the incidence of serious arrhythmias and conduction disturbances reported as adverse events in the DIAMOND subpopulation that had AF at entry to these trials.

Table 7: Incidence of Serious Arrhythmias and Conduction Disturbances in Patients with AF at Entry to the DIAMOND Studies
 | TIKOSYN | Placebo
 | N=249 | N=257
Ventricular arrhythmias [Patients with more than one arrhythmia are counted only once in this category.] [Ventricular arrhythmias and ventricular tachycardia include all cases of Torsade de Pointes.] | 14.5% | 13.6%
Ventricular fibrillation | 4.8% | 3.1%
Ventricular tachycardia | 12.4% | 11.3%
Torsade de Pointes | 1.6% | 0
Various forms of block
AV block | 0.8% | 2.7%
(Left) bundle branch block | 0 | 0.4%
Heart block | 1.2% | 0.8%

Other Adverse Reactions:

Table 8 presents other adverse events reported with a frequency of >2% on TIKOSYN and reported numerically more frequently on TIKOSYN than on placebo in the studies of patients with supraventricular arrhythmias.

Table 8: Frequency of Adverse Events Occurring at >2% on TIKOSYN, and Numerically More Frequently on TIKOSYN than Placebo in Patients with Supraventricular Arrhythmias
 | TIKOSYN | Placebo
Adverse Event | % | %
headache | 11 | 9
chest pain | 10 | 7
dizziness | 8 | 6
respiratory tract infection | 7 | 5
dyspnea | 6 | 5
nausea | 5 | 4
flu syndrome | 4 | 2
insomnia | 4 | 3
accidental injury | 3 | 1
back pain | 3 | 2
procedure (medical/surgical/health service) | 3 | 2
diarrhea | 3 | 2
rash | 3 | 2
abdominal pain | 3 | 2

Adverse events reported at a rate >2% but no more frequently on TIKOSYN than on placebo were: angina pectoris, anxiety, arthralgia, asthenia, atrial fibrillation, complications (application, injection, incision, insertion, or device), hypertension, pain, palpitation, peripheral edema, supraventricular tachycardia, sweating, urinary tract infection, ventricular tachycardia.

The following adverse events have been reported with a frequency of ≤2% and numerically more frequently with TIKOSYN than placebo in patients with supraventricular arrhythmias: angioedema, bradycardia, cerebral ischemia, cerebrovascular accident, edema, facial paralysis, flaccid paralysis, heart arrest, increased cough, liver damage, migraine, myocardial infarct, paralysis, paresthesia, sudden death, and syncope.

The incidences of clinically significant laboratory test abnormalities in patients with supraventricular arrhythmias were similar for patients on TIKOSYN and those on placebo. No clinically relevant effects were noted in serum alkaline phosphatase, serum GGT, LDH, AST, ALT, total bilirubin, total protein, blood urea nitrogen, creatinine, serum electrolytes (calcium, chloride, glucose, magnesium, potassium, sodium), or creatine kinase. Similarly, no clinically relevant effects were observed in hematologic parameters.

In the DIAMOND population, adverse events other than those related to the post-infarction and heart failure patient population were generally similar to those seen in the supraventricular arrhythmia groups.

OVERDOSAGE

There is no known antidote to TIKOSYN; treatment of overdose should therefore be symptomatic and supportive. The most prominent manifestation of overdosage is likely to be excessive prolongation of the QT interval.

In cases of overdose, cardiac monitoring should be initiated. Charcoal slurry may be given soon after overdosing but has been useful only when given within 15 minutes of TIKOSYN administration. Treatment of Torsade de Pointes or overdose may include administration of isoproterenol infusion, with or without cardiac pacing. Administration of intravenous magnesium sulfate may be effective in the management of Torsade de Pointes. Close medical monitoring and supervision should continue until the QT interval returns to normal levels.

Isoproterenol infusion into anesthetized dogs with cardiac pacing rapidly attenuates the dofetilide-induced prolongation of atrial and ventricular effective refractory periods in a dose-dependent manner. Magnesium sulfate, administered prophylactically either intravenously or orally in a dog model, was effective in the prevention of dofetilide-induced Torsade de Pointes ventricular tachycardia. Similarly, in man, intravenous magnesium sulfate may terminate Torsade de Pointes, irrespective of cause.

TIKOSYN overdose was rare in clinical studies; there were two reported cases of TIKOSYN overdose in the oral clinical program. One patient received very high multiples of the recommended dose (28 capsules), was treated with gastric aspiration 30 minutes later, and experienced no events. One patient inadvertently received two 500 mcg doses one hour apart and experienced ventricular fibrillation and cardiac arrest 2 hours after the second dose.

In the supraventricular arrhythmia population, only 38 patients received doses greater than 500 mcg BID, all of whom received 750 mcg BID irrespective of creatinine clearance. In this very small patient population, the incidence of Torsade de Pointes was 10.5% (4/38 patients), and the incidence of new ventricular fibrillation was 2.6% (1/38 patients).

DOSAGE AND ADMINISTRATION

- Therapy with TIKOSYN must be initiated (and, if necessary, re-initiated) in a setting that provides continuous electrocardiographic (ECG) monitoring and in the presence of personnel trained in the management of serious ventricular arrhythmias. Patients should continue to be monitored in this way for a minimum of three days. Additionally, patients should not be discharged within 12 hours of electrical or pharmacological conversion to normal sinus rhythm.
- The dose of TIKOSYN must be individualized according to calculated creatinine clearance and QTc. (QT interval should be used if the heart rate is <60 beats per minute. There are no data on use of TIKOSYN when the heart rate is <50 beats per minute.) The usual recommended dose of TIKOSYN is 500 mcg BID, as modified by the dosing algorithm described below. For consideration of a lower dose, see Special Considerations below.
- Serum potassium should be maintained within the normal range before TIKOSYN treatment is initiated and should be maintained within the normal range while the patient remains on TIKOSYN therapy. (See WARNINGS, Hypokalemia and Potassium-Depleting Diuretics). In clinical trials, potassium levels were generally maintained above 3.6–4.0 mEq/L.
- Patients with atrial fibrillation should be anticoagulated according to usual medical practice prior to electrical or pharmacological cardioversion. Anticoagulant therapy may be continued after cardioversion according to usual medical practice for the treatment of people with AF. Hypokalemia should be corrected before initiation of TIKOSYN therapy (see WARNINGS, Ventricular Arrhythmia).
- Patients to be discharged on TIKOSYN therapy from an inpatient setting as described above must have an adequate supply of TIKOSYN, at the patient's individualized dose, to allow uninterrupted dosing until the patient can fill a TIKOSYN prescription.

Instructions for Individualized Dose Initiation

Initiation of TIKOSYN Therapy

Step 1. Electrocardiographic assessment: Prior to administration of the first dose, the QTc or QT must be checked using an average of 5–10 beats. If the QTc or QT is greater than 440 msec (500 msec in patients with ventricular conduction abnormalities), TIKOSYN is contraindicated. If heart rate is less than 60 beats per minute, QT interval should be used. Proceed to Step 2 if the QTc or QT is 440 msec. Patients with heart rates <50 beats per minute have not been studied.

Step 2. Calculation of creatinine clearance: Prior to the administration of the first dose, the patient's creatinine clearance must be calculated using the following formula:

creatinine clearance (male) = | (140-age) × actual body weight in kg 72 × serum creatinine (mg/dL)
creatinine clearance (female) = | (140-age) × actual body weight in kg × 0.85 72 × serum creatinine (mg/dL)

When serum creatinine is given in µmol/L, divide the value by 88.4 (1 mg/dL = 88.4 µmol/L).

Step 3. Starting Dose: The starting dose of TIKOSYN is determined as follows:

Calculated Creatinine Clearance | TIKOSYN Dose
>60 mL/min | 500 mcg twice daily
40 to 60 mL/min | 250 mcg twice daily
20 to <40 mL/min | 125 mcg twice daily
<20 mL/min | Tikosyn is contraindicated in these patients

Step 4. Administer the adjusted TIKOSYN dose and begin continuous ECG monitoring.

Step 5. At 2–3 hours after administering the first dose of Tikosyn, determine the QTc or QT (if heart rate is less than 60 beats per minute). If the QTc or QT has increased by greater than 15% compared to the baseline established in Step 1 OR if the QTc or QT is greater than 500 msec (550 msec in patients with ventricular conduction abnormalities), subsequent dosing should be adjusted as follows:

If the Starting Dose Based on Creatinine Clearance is: |  | Then the Adjusted Dose (for QTc or QT Prolongation) is:
500 mcg twice daily |  | 250 mcg twice daily
250 mcg twice daily |  | 125 mcg twice daily
125 mcg twice daily |  | 125 mcg once a day

Step 6. At 2–3 hours after each subsequent dose of Tikosyn, determine the QTc or QT (if heart rate is less than 60 beats per minute) (for in-hospital doses 2–5). No further down titration of Tikosyn based on QTc or QT is recommended.

NOTE: If at any time after the second dose of Tikosyn is given the QTc or QT is greater than 500 msec (550 msec in patients with ventricular conduction abnormalities), Tikosyn should be discontinued.

Step 7. Patients are to be continuously monitored by ECG for a minimum of three days, or for a minimum of 12 hours after electrical or pharmacological conversion to normal sinus rhythm, whichever is greater.

The steps described above are summarized in the following diagram:

Maintenance of TIKOSYN Therapy

Renal function and QTc or QT (if heart rate is less than 60 beats per minute) should be re-evaluated every three months or as medically warranted. If QTc or QT exceeds 500 milliseconds (550 msec in patients with ventricular conduction abnormalities), TIKOSYN therapy should be discontinued and patients should be carefully monitored until QTc or QT returns to baseline levels. If renal function deteriorates, adjust dose as described in Initiation of TIKOSYN Therapy, Step 3.

Special Considerations

Consideration of a Dose Lower than that Determined by the Algorithm:

The dosing algorithm shown above should be used to determine the individualized dose of TIKOSYN. In clinical trials (see CLINICAL STUDIES), the highest dose of 500 mcg BID of TIKOSYN as modified by the dosing algorithm led to greater effectiveness than lower doses of 125 or 250 mcg BID as modified by the dosing algorithm. The risk of Torsade de Pointes, however, is related to dose as well as to patient characteristics (see WARNINGS). Physicians, in consultation with their patients, may therefore in some cases choose doses lower than determined by the algorithm. It is critically important that if at any time this lower dose is increased, the patient needs to be rehospitalized for three days. Previous toleration of higher doses does not eliminate the need for rehospitalization.

The maximum recommended dose in patients with a calculated creatinine clearance greater than 60 mL/min is 500 mcg BID; doses greater than 500 mcg BID have been associated with an increased incidence of Torsade de Pointes.

A patient who misses a dose should NOT double the next dose. The next dose should be taken at the usual time.

Cardioversion:

If patients do not convert to normal sinus rhythm within 24 hours of initiation of TIKOSYN therapy, electrical conversion should be considered. Patients continuing on TIKOSYN after successful electrical cardioversion should continue to be monitored by electrocardiography for 12 hours post cardioversion, or a minimum of 3 days after initiation of TIKOSYN therapy, whichever is greater.

Switch to TIKOSYN from Class I or other Class III Antiarrhythmic Therapy

Before initiating TIKOSYN therapy, previous antiarrhythmic therapy should be withdrawn under careful monitoring for a minimum of three (3) plasma half-lives. Because of the unpredictable pharmacokinetics of amiodarone, TIKOSYN should not be initiated following amiodarone therapy until amiodarone plasma levels are below 0.3 mcg/mL or until amiodarone has been withdrawn for at least three months.

Stopping TIKOSYN Prior to Administration of Potentially Interacting Drugs

If TIKOSYN needs to be discontinued to allow dosing of other potentially interacting drug(s), a washout period of at least two days should be followed before starting the other drug(s).

HOW SUPPLIED

TIKOSYN® 125 mcg (0.125 mg) capsules are supplied as No. 4 capsules with a light orange cap and white body, printed with TKN 125 PFIZER, and are available in:

TIKOSYN® 250 mcg (0.25 mg) capsules are supplied as No. 4 capsules, peach cap and body, printed with TKN 250 PFIZER, and are available in:

TIKOSYN® 500 mcg (0.5 mg) capsules are supplied as No. 2 capsules, peach cap and white body, printed with TKN 500 PFIZER, and are available in:

 | 125 mcg (0.125 mg) | 250 mcg (0.25 mg) | 500 mcg (0.5 mg)
Obverse | TKN 125 | TKN 250 | TKN 500
Reverse | PFIZER | PFIZER | PFIZER
Bottle of 14 | 0069-5800-61 | 0069-5810-61 | 0069-5820-61
Bottle of 60 | 0069-5800-60 | 0069-5810-60 | 0069-5820-60
Unit dose / 40 | 0069-5800-43 | 0069-5810-43 | 0069-5820-43

STORAGE AND HANDLING

Store at controlled room temperature, 15° to 30°C (59° to 86°F).

PROTECT FROM MOISTURE AND HUMIDITY.

Dispense in tight containers (USP).

Rx only

LAB-0067-11.0

Revised August 2023

MEDICATION GUIDE

TIKOSYN® (Tee' ko sin)
(dofetilide) Capsules

Read the Medication Guide before you start taking TIKOSYN and each time you get a refill. This information does not take the place of talking with your doctor about your condition or treatment.

What is the most important information I should know about TIKOSYN?

TIKOSYN can cause serious side effects, including a type of abnormal heartbeat called Torsade de Pointes, which can lead to death.

To establish the right dose of TIKOSYN, treatment with TIKOSYN must be started in a hospital where your heart rate and kidney function will be checked for the first 3 days of treatment. It is important that when you go home, you take the exact dose of TIKOSYN that your doctor prescribed for you.

While you take TIKOSYN, always watch for signs of abnormal heartbeat.

Call your doctor and go to the hospital right away if you:

- feel faint
- become dizzy, or
- have a fast heartbeat

What is TIKOSYN?

TIKOSYN is a prescription medicine that is used to treat an irregular heartbeat (atrial fibrillation or atrial flutter).

It is not known if TIKOSYN is safe and effective in children under 18 years of age.

Who should not take TIKOSYN?

Do not take TIKOSYN if you:

- have an irregular heartbeat called long QT syndrome
- have kidney problems or are on kidney dialysis
- take any of these medicines:
  - cimetidine (TAGAMET, TAGAMET HB) [Listed trademarks are the property of their respective owners.]
  - verapamil (CALAN, CALAN SR, COVERA-HS, ISOPTIN, ISOPTIN SR, VERELAN, VERELAN PM, TARKA)
  - ketoconazole (NIZORAL, XOLEGEL, EXTINA)
  - trimethoprim alone (PROLOPRIM, TRIMPEX) or the combination of trimethoprim and sulfamethoxazole (BACTRIM, SEPTRA SULFATRIM)
  - prochlorperazine (COMPAZINE, COMPO)
  - megestrol (MEGACE)
  - dolutegravir (TIVICAY)
  - hydrochlorothiazide alone or in combination with other medicines (such as ESIDRIX, EZIDE, HYDRODIURIL, HYDRO-PAR, MICROZIDE, or ORETIC)
Ask your doctor if you are not sure if any of your medicines are the kind listed above.
- are allergic to dofetilide in TIKOSYN. See the end of this leaflet for a complete list of ingredients in TIKOSYN.

What should I tell my doctor before taking TIKOSYN?

Before taking TIKOSYN, tell your doctor about all of your medical conditions including if you:

- have heart problems
- have kidney or liver problems
- are pregnant or plan to become pregnant. It is not known if TIKOSYN will harm your unborn baby.
- are breast-feeding or plan to breast-feed. It is not known if TIKOSYN passes into your breast milk. You and your doctor should decide if you will take TIKOSYN or breast-feed. You should not do both.

Especially tell your doctor if you take medicines to treat:

- heart problems
- high blood pressure
- depression or other mental problems
- asthma
- allergies, or hay fever
- skin problems
- infections

Ask your doctor if you are not sure about the medicines you take. Tell your doctor about all prescription and non-prescription medicines, vitamins, dietary supplements, and any natural or herbal remedies. TIKOSYN and other medicines may affect each other, causing serious side effects. If you take TIKOSYN with certain medicines, you will be more likely to have a different type of abnormal heartbeat. See "Who should not take TIKOSYN?"

Know the medicines you take. Keep a list of your medicines and show it to your doctor and pharmacist when you get a new medicine.

How should I take TIKOSYN?

- Take TIKOSYN exactly as your doctor tells you.
- Do not change your TIKOSYN dose unless your doctor tells you to.
- Your doctor will do tests before you start and while you take TIKOSYN.
- Do not stop taking TIKOSYN until your doctor tells you to stop. If you miss a dose, just take the next dose at your regular time. Do not take 2 doses of TIKOSYN at the same time.
- TIKOSYN can be taken with or without food.
- If you take too much TIKOSYN, call your doctor or go to the nearest hospital emergency room right away. Take your TIKOSYN capsules with you to show to the doctor.

What are the possible side effects of TIKOSYN?

TIKOSYN can cause serious side effects, including a type of abnormal heartbeat called Torsade de Pointes, which can lead to death. See "What is the most important information I should know about TIKOSYN?"

The most common side effects of TIKOSYN include:

- headache
- chest pain
- dizziness

Call your doctor right away if you have signs of electrolyte imbalance:

- severe diarrhea
- unusual sweating
- vomiting
- not hungry (loss of appetite)
- increased thirst (drinking more than normal)

Tell your doctor if you have any side effects that bother you or do not go away.

These are not all the possible side effects of TIKOSYN. For more information, ask your doctor or pharmacist. Call your doctor for medical advice about side effects. You may report side effects to FDA at 1-800-FDA-1088.

How should I store TIKOSYN?

- Store TIKOSYN between 59° to 86°F (15° to 30°C).
- Keep TIKOSYN away from moisture and humidity.
- Keep TIKOSYN in a tightly closed container.
- Keep TIKOSYN and all medicines out of the reach of children.

General information about TIKOSYN

Medicines are sometimes prescribed for purposes other than those listed in a Medication Guide. Do not use TIKOSYN for a condition for which it was not prescribed. Do not give TIKOSYN to other people, even if they have the same symptoms you have. It may harm them.

This Medication Guide summarizes the most important information about TIKOSYN. If you would like more information, talk with your doctor. You can ask your doctor or pharmacist for information about TIKOSYN that is written for health professionals.

For more about TIKOSYN, go to www.tikosyn.com or call 1-877-TIKOSYN (1-877-845-6796).

What are the ingredients in TIKOSYN?

Active ingredient: dofetilide

Inactive ingredients:

Capsule fill: microcrystalline cellulose, corn starch, colloidal silicon dioxide, and magnesium stearate
Capsule shell: gelatin, titanium dioxide, and FD&C Yellow 6
Imprinting ink: iron oxide black, shellac, n-butyl alcohol, isopropyl alcohol, propylene glycol, and ammonium hydroxide

Rx only

LAB-0405-4.0

Revised August 2023

This Medication Guide has been approved by the U.S. Food and Drug Administration.

PRINCIPAL DISPLAY PANEL - 0.125 mg Capsule Bottle Label

ALWAYS DISPENSE WITH MEDICATION GUIDE

Pfizer
NDC 0069-5800-60

Tikosyn®

(dofetilide) Capsules

125 mcg (0.125 mg)

60 Capsules
Rx only

PRINCIPAL DISPLAY PANEL - 0.125 mg Capsule Blister Pack

FOR INSTITUTION USE

Tikosyn®

(dofetilide) Capsule

125mcg (0.125mg)

PFIZER LABS
DIV. OF PFIZER INC., New York, NY 10001
PAA214098

LOT: XXXXXXX
EXP: YYYY-MMM

PRINCIPAL DISPLAY PANEL - 0.125 mg Capsule Blister Pack Carton

ALWAYS DISPENSE WITH MEDICATION GUIDE

Pfizer
NDC 0069-5800-43

Tikosyn®

(dofetilide) capsules

125 mcg (0.125 mg)

For in-institution use only

40 Capsules

Rx only
UNIT DOSE

PRINCIPAL DISPLAY PANEL - 0.25 mg Capsule Bottle Label

ALWAYS DISPENSE WITH MEDICATION GUIDE

Pfizer
NDC 0069-5810-60

Tikosyn®

(dofetilide) Capsules

250 mcg (0.25 mg)

60 Capsules
Rx only

PRINCIPAL DISPLAY PANEL - 0.25 mg Capsule Blister Pack

FOR INSTITUTION USE

Tikosyn®

(dofetilide) Capsule

250mcg (0.25mg)

PFIZER LABS
DIV. OF PFIZER INC., New York, NY 10001
PAA214096

LOT: XXXXXXX
EXP: YYYY-MMM

PRINCIPAL DISPLAY PANEL - 0.25 mg Capsule Blister Pack Carton

ALWAYS DISPENSE WITH MEDICATION GUIDE

Pfizer
NDC 0069-5810-43

Tikosyn®

(dofetilide) capsules

250 mcg (0.25 mg)

For in-institution use only

40 Capsules

Rx only
UNIT DOSE

PRINCIPAL DISPLAY PANEL - 0.5 mg Capsule Bottle Label

ALWAYS DISPENSE WITH MEDICATION GUIDE

Pfizer
NDC 0069-5820-60

Tikosyn®

(dofetilide) Capsules

500 mcg (0.5 mg)

60 Capsules
Rx only

PRINCIPAL DISPLAY PANEL - 0.5 mg Capsule Blister Pack

FOR INSTITUTION USE

Tikosyn®

(dofetilide) Capsule

500mcg (0.5mg)

PFIZER LABS
DIV. OF PFIZER INC., New York, NY 10001
PAA214097

LOT: XXXXXXX
EXP: YYYY-MMM

PRINCIPAL DISPLAY PANEL - 0.5 mg Capsule Blister Pack Carton

ALWAYS DISPENSE WITH MEDICATION GUIDE

Pfizer
NDC 0069-5820-43

Tikosyn®

(dofetilide) capsules

500 mcg (0.5 mg)

For in-institution use only

40 Capsules

Rx only
UNIT DOSE